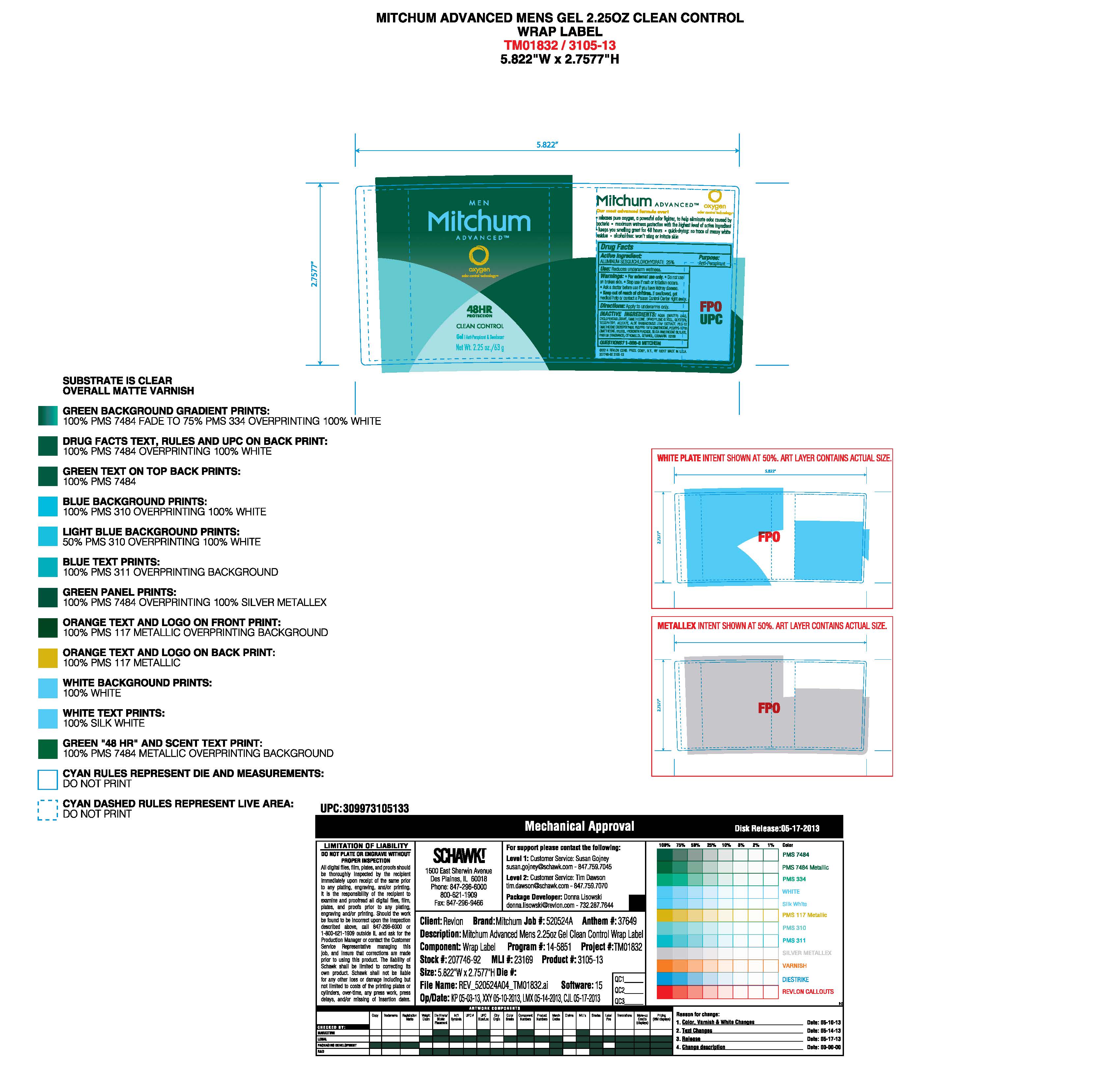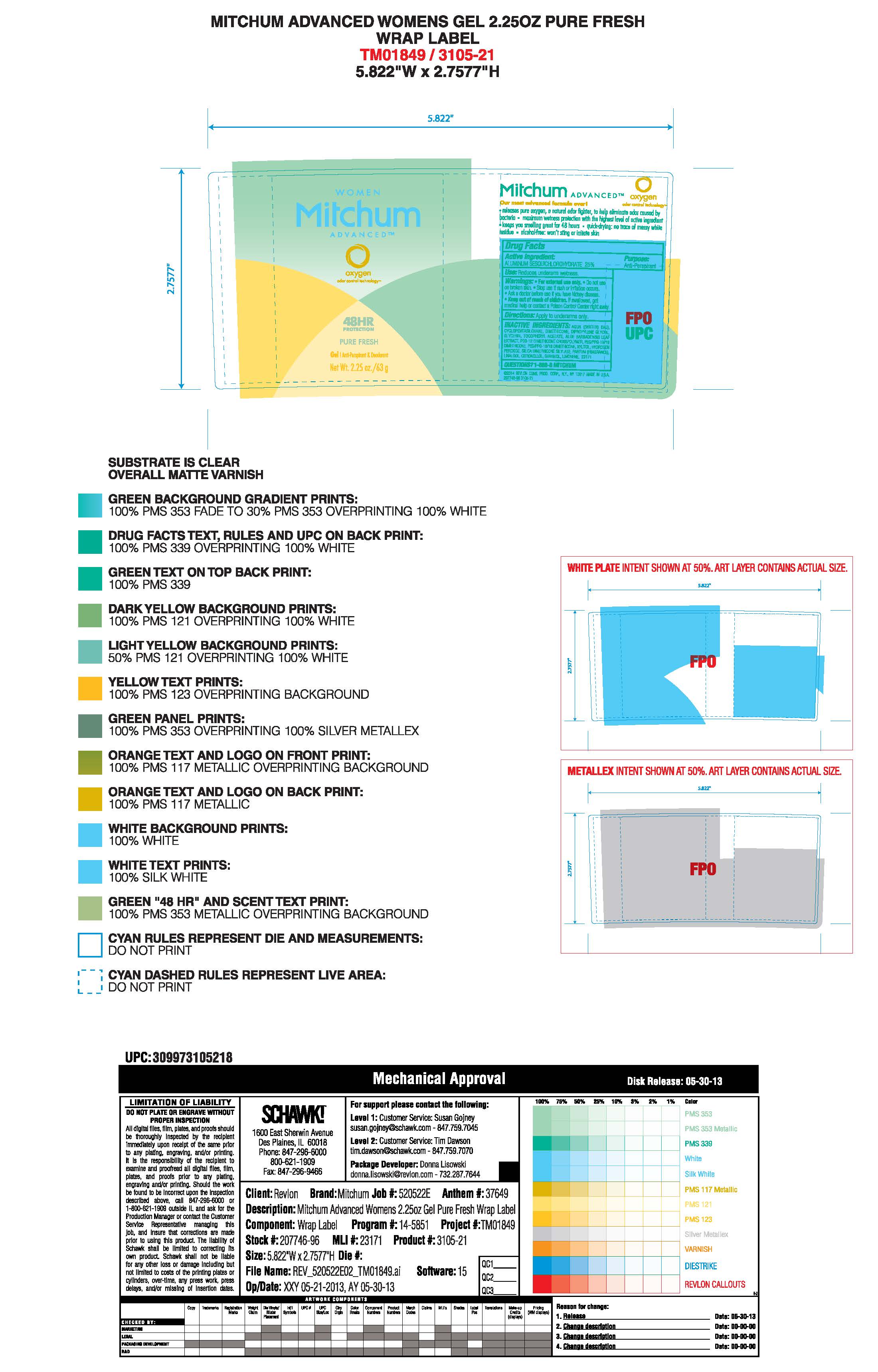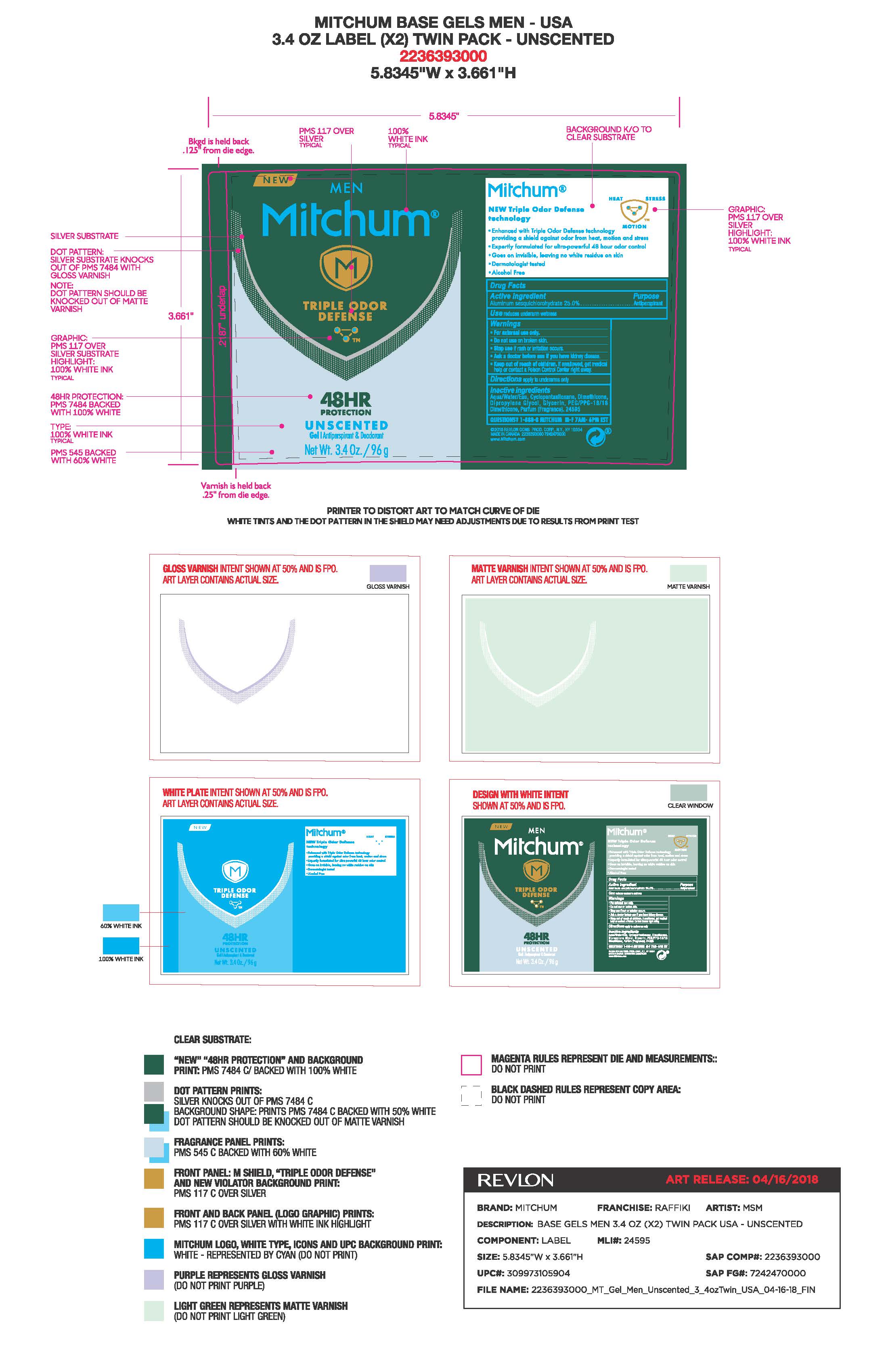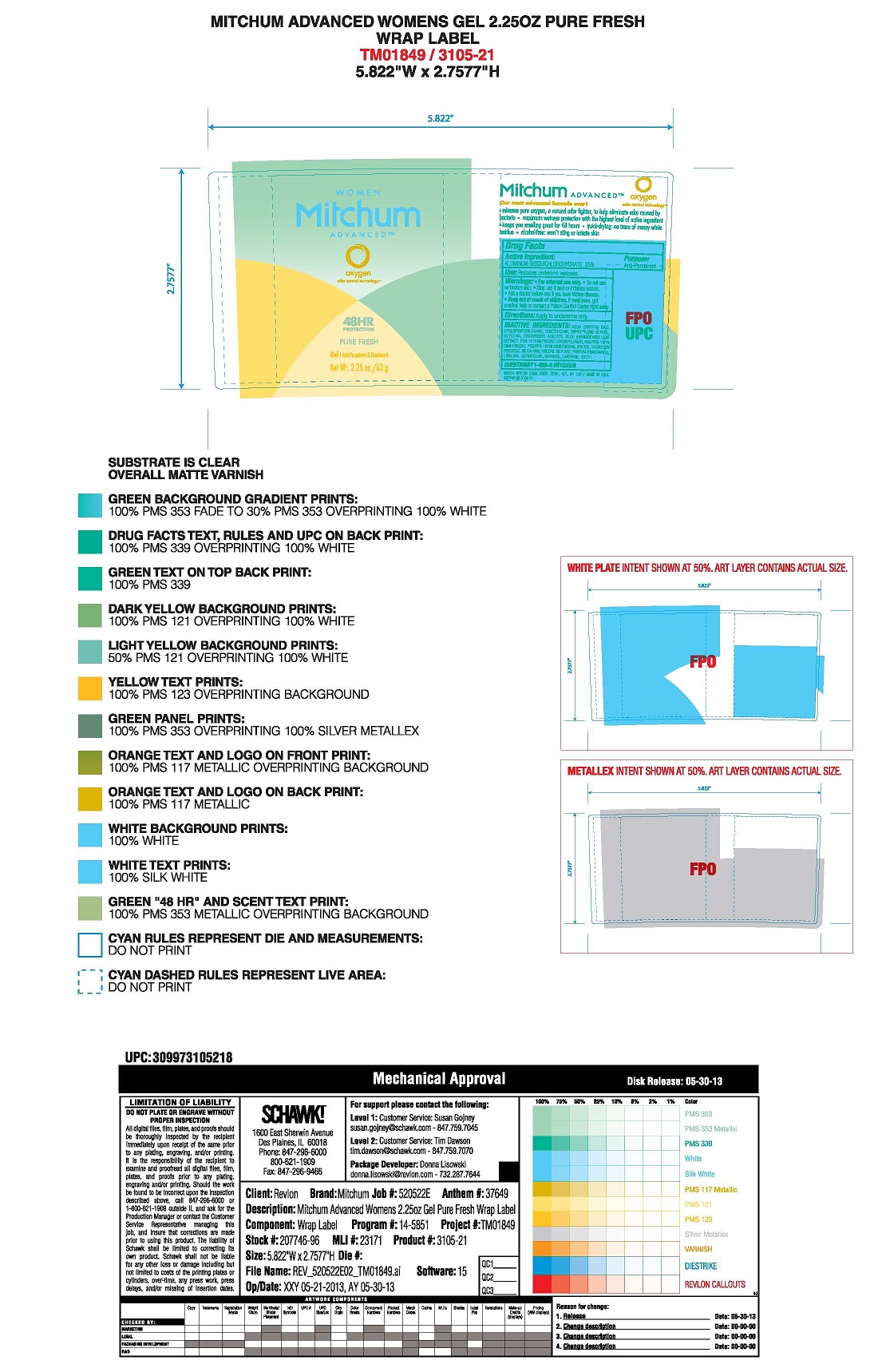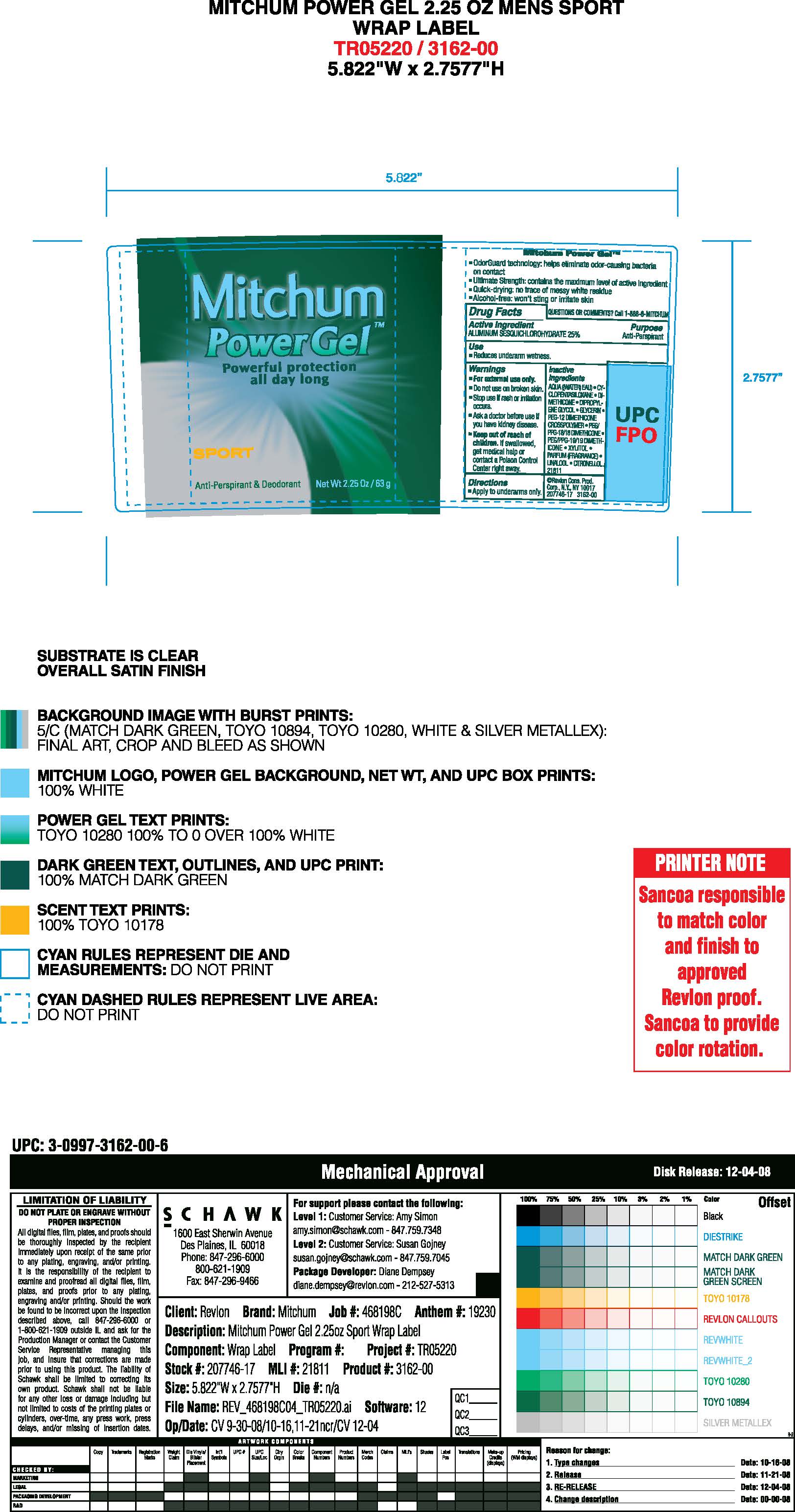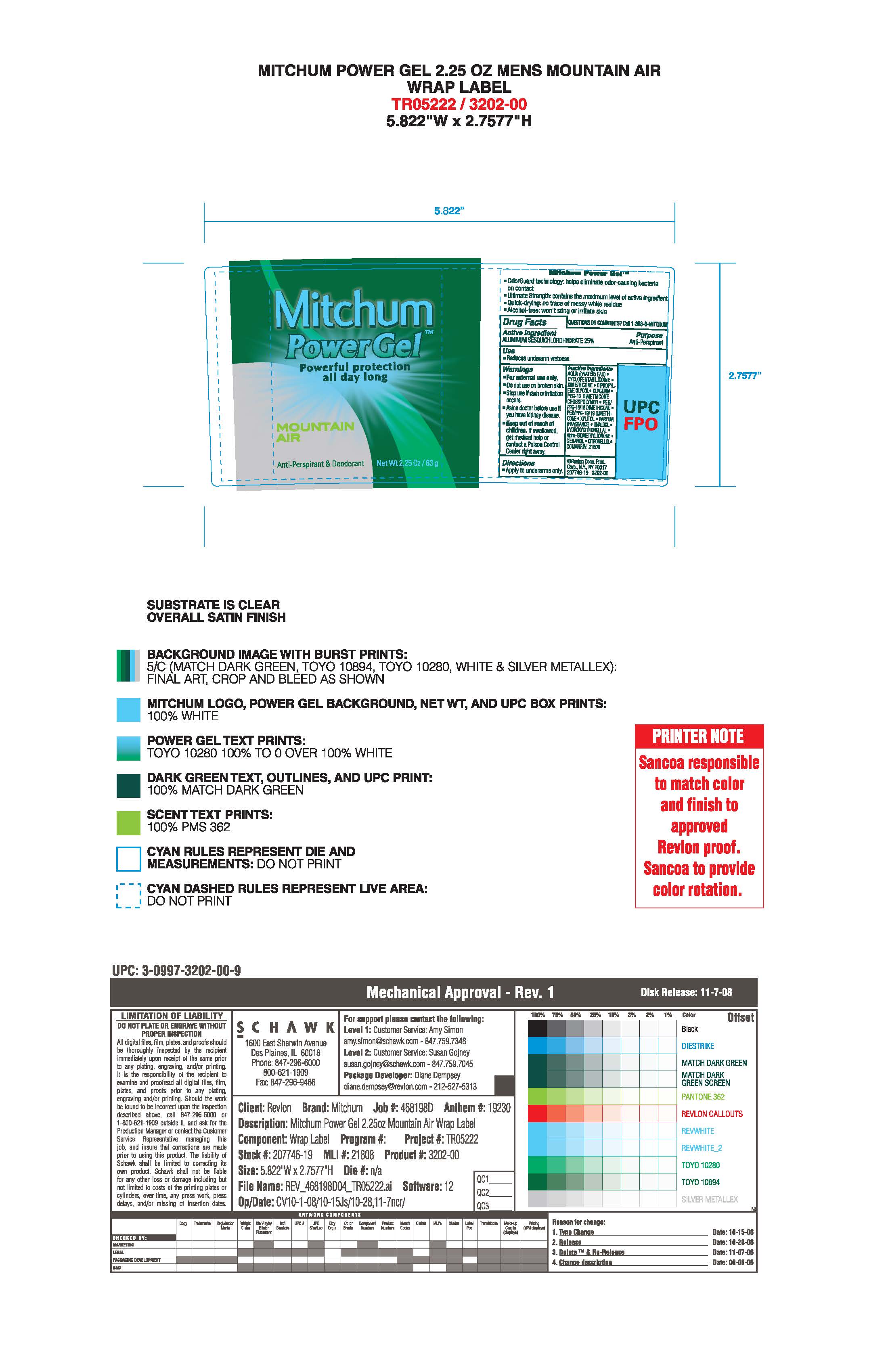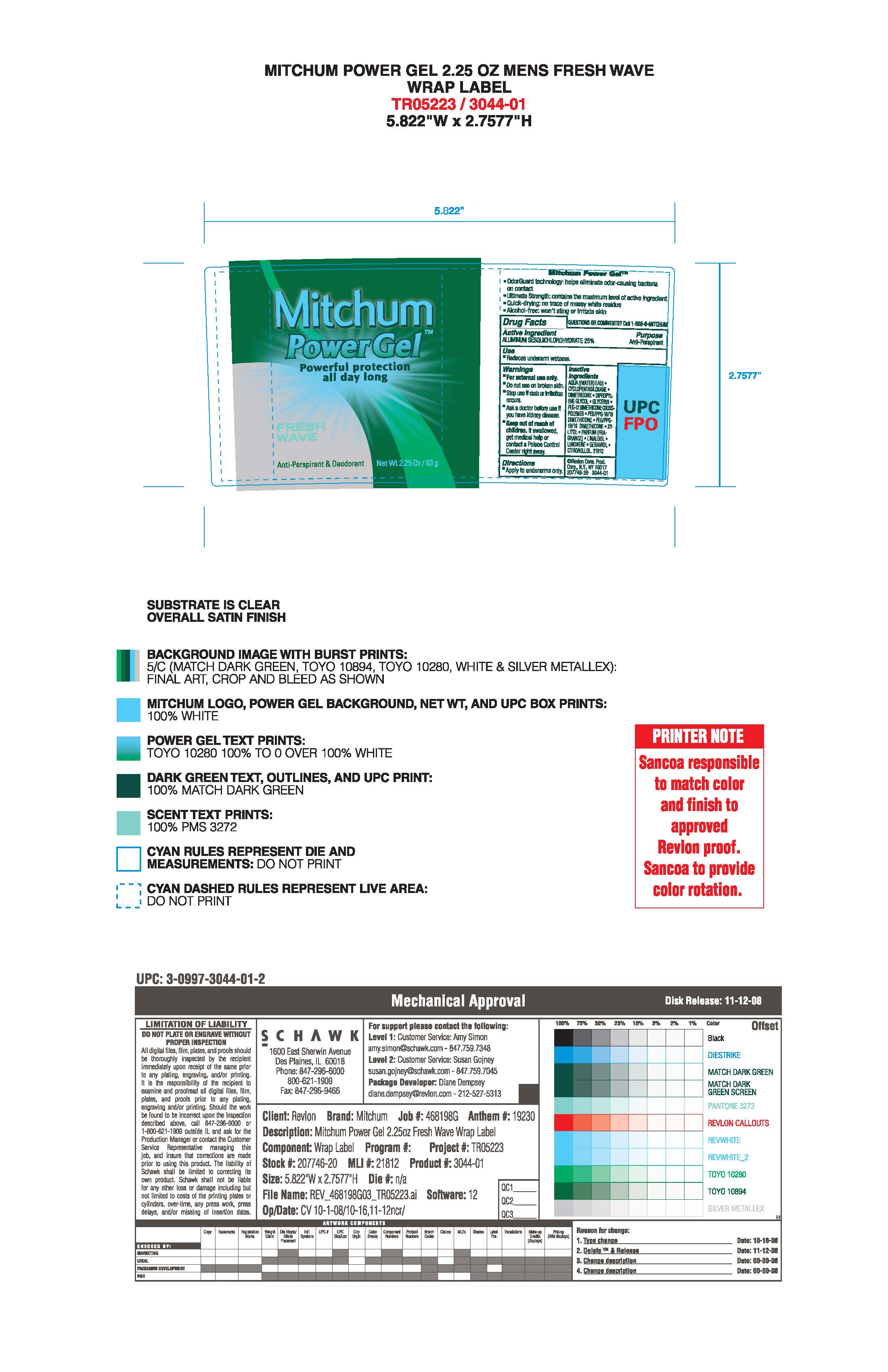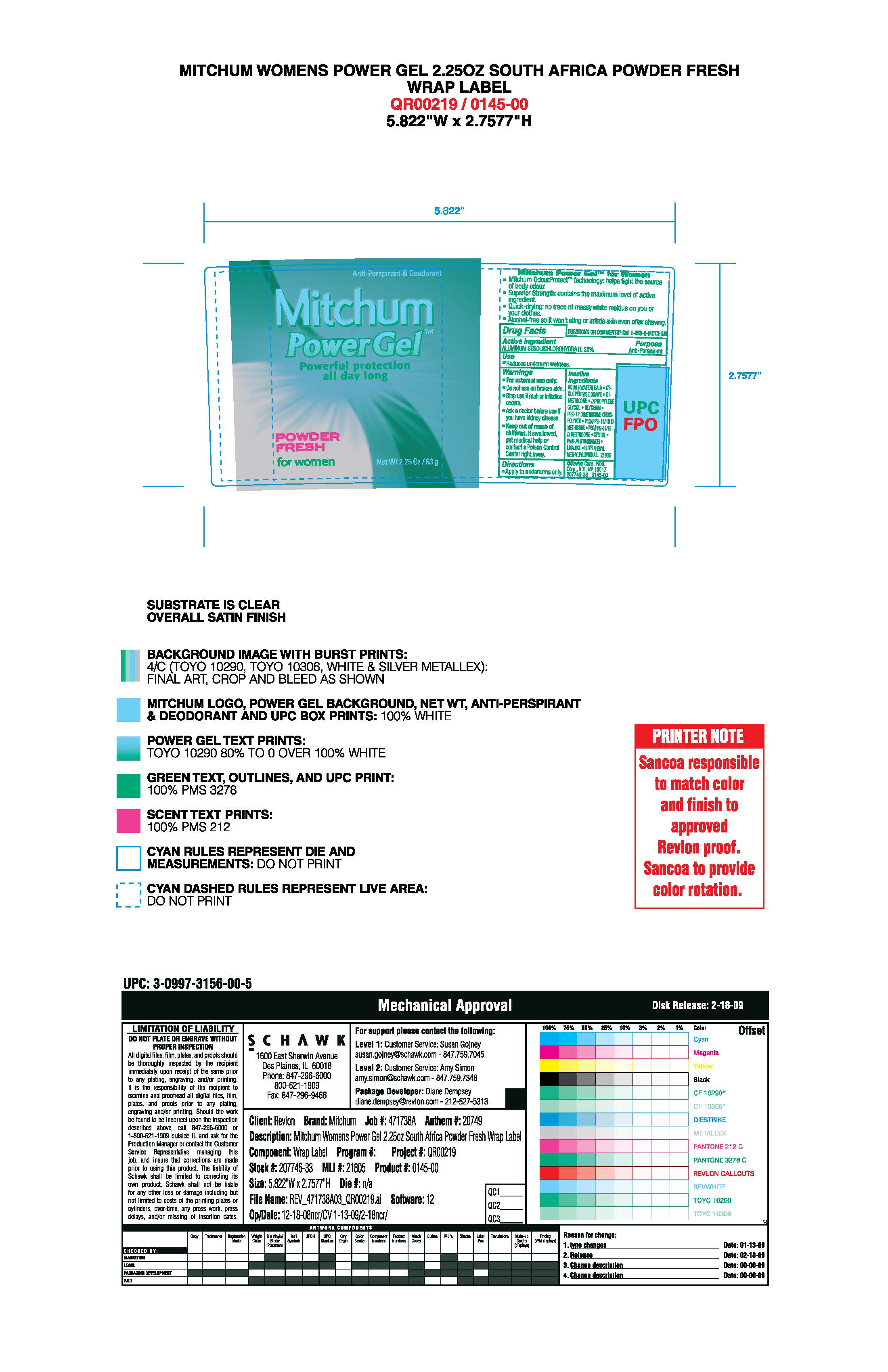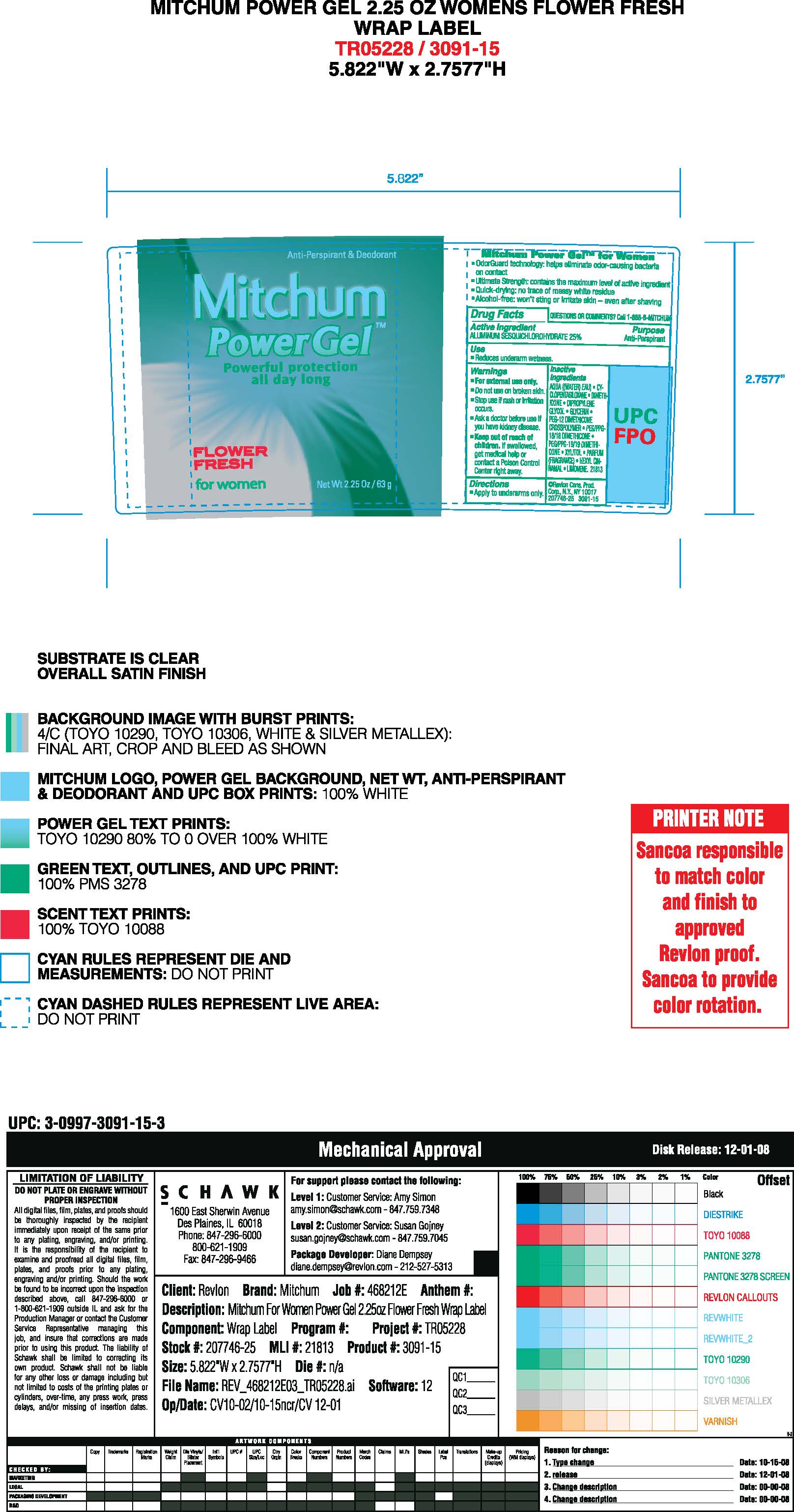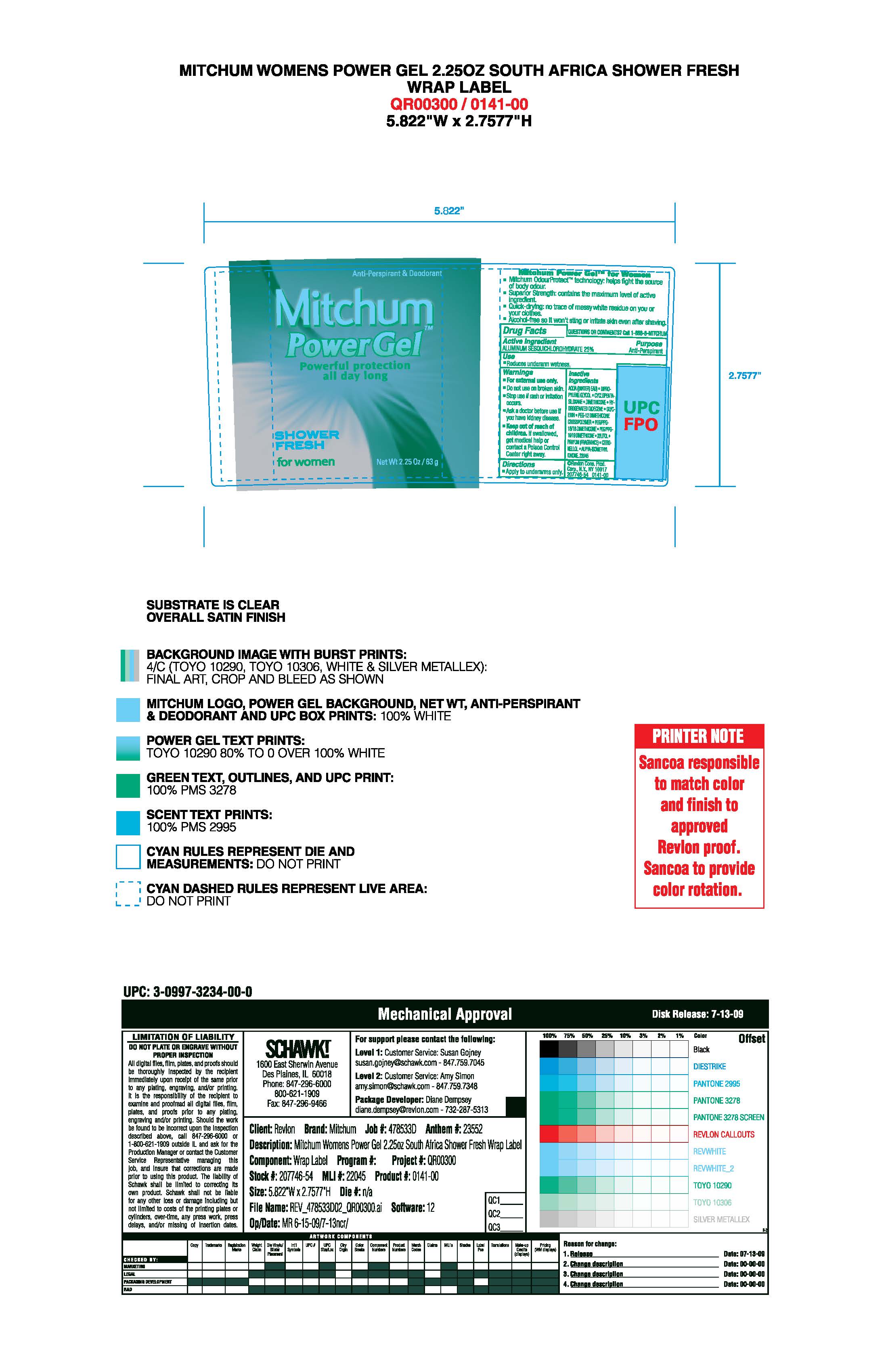 DRUG LABEL: Mitchum Clear Gel
NDC: 10967-603 | Form: LIQUID
Manufacturer: Revlon Consumer Products Corp
Category: otc | Type: HUMAN OTC DRUG LABEL
Date: 20251229

ACTIVE INGREDIENTS: ALUMINUM SESQUICHLOROHYDRATE 0.25 g/1 mL
INACTIVE INGREDIENTS: WATER; CYCLOMETHICONE 5; DIMETHICONE; GLYCERIN; PEG-12 DIMETHICONE; PEG/PPG-19/19 DIMETHICONE; PEG/PPG-18/18 DIMETHICONE; DIPROPYLENE GLYCOL; .BETA.-CITRONELLOL, (R)-; LINALOOL, (+/-)-

Mitchum Clear Gel AP

ACTIVE INGREDIENT

Aluminum Sesquicholorhydrate 25%

Purpose

Antiperspirant

Warnings:

For external use only.

Do not use on broken skin

Ask a doctor before use if you have kidney disease

Stop use if rash or irriation occurs

KEEP OUT OF REACH OF CHILDREN

If swallowed, get medical help or contact a Poison Control Center right away.

Inactive Ingredients

AQUA ((WATER) EAU) , CYCLOPENTASILOXANE, DIMETHICONE, DIPROPYLENE GLYCOL, GLYCERIN , PARFUM (FRAGRANCE) , PEG-12 DIMETHICONE CROSSPOLYMER, PEG/PPG-19/19 DIMETHICONE, PEG/PPG-18/18 DIMETHICONE, LINALOOL, XYLITOL, CITRONELLOL

INDICATIONS AND USAGE

Reduces underarm wetness